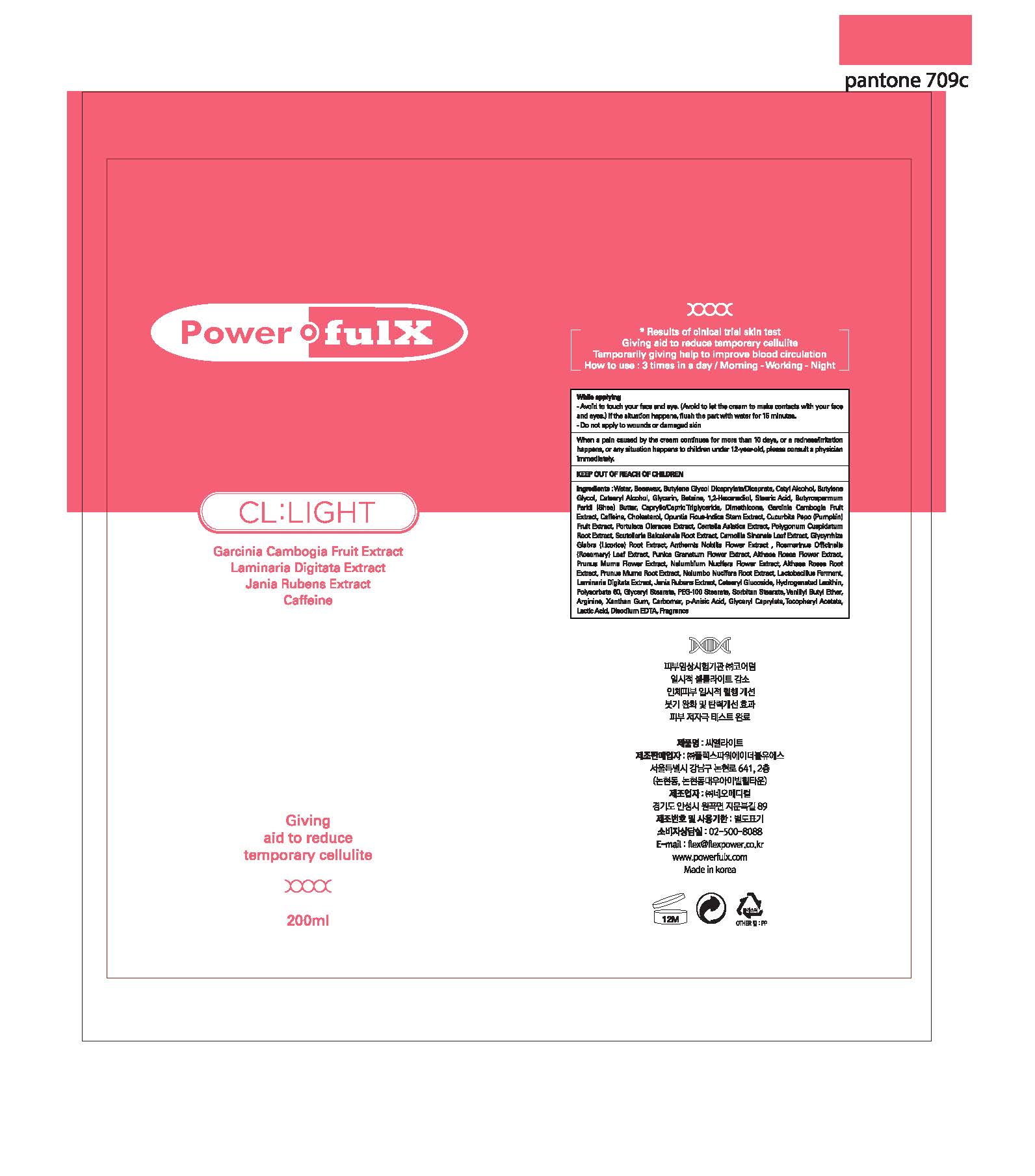 DRUG LABEL: CL LIGHT
NDC: 70042-0003 | Form: CREAM
Manufacturer: Powerful X
Category: otc | Type: HUMAN OTC DRUG LABEL
Date: 20180830

ACTIVE INGREDIENTS: CAFFEINE 0.63 g/100 mL; GARCINIA GUMMI-GUTTA FRUIT 0.04 g/100 mL
INACTIVE INGREDIENTS: WATER

Drug Facts

ACTIVE INGREDIENT

Garcinia Cambogia Fruit Extract, Caffeine

INACTIVE INGREDIENT

Jania Rubens Extract, Laminaria Digitata Extract, Water, etc.

PURPOSE

Giving aid to reduce temporary cellulite

keep out of reach of the children

WARNINGS

Consult a physician if you have any abnormal symptoms such as red spots, swelling or itching, or side effects caused by direct sunlight.

DOSAGE AND ADMINISTRATION

for external use only

INDICATIONS AND USAGE

Apply it as a massge befor exercie, after shower.